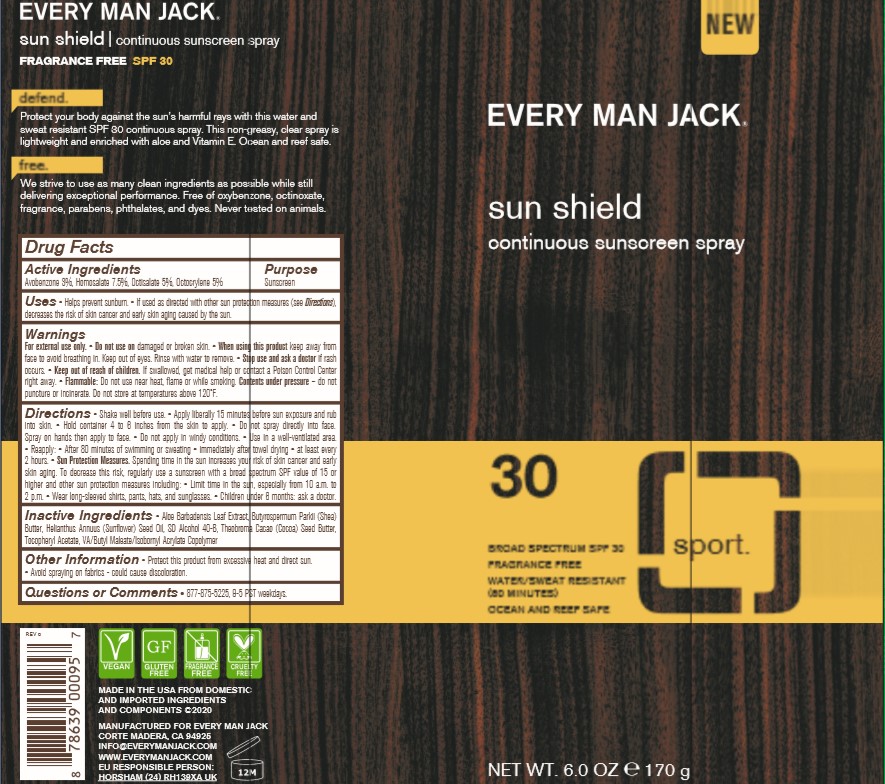 DRUG LABEL: Every Man Jack
NDC: 13630-0164 | Form: SPRAY
Manufacturer: Prime Packaging, Inc.
Category: otc | Type: HUMAN OTC DRUG LABEL
Date: 20201012

ACTIVE INGREDIENTS: AVOBENZONE 3 g/100 g; HOMOSALATE 7.5 g/100 g; OCTISALATE 5 g/100 g; OCTOCRYLENE 5 g/100 g
INACTIVE INGREDIENTS: COCOA BUTTER; ALOE VERA LEAF; .ALPHA.-TOCOPHEROL ACETATE; ISOBORNYL ACRYLATE; ALCOHOL; VINYL ACETATE; DIBUTYL MALEATE; SUNFLOWER OIL; SHEA BUTTER

Every Man Jack sunscreen spray Broad Spectrum SPF 30

Active Ingredients

Avobenzone 3%

Homosalate 7.5%

Octisalate 5%

Octocrylene 5%

Purpose

Sunscreen

Uses

- Helps prevent sunburn.
- If used as directed with other sun protection measures (see Directions), decreases the risk of skin cancer and early skin aging caused by the sun.

Warnings

For external use only.

Do not use on damaged or broken skin

When using this product Keep away from face to avoid breathing it. keep out of eyes. Rinse with water to remove.

Stop use and ask a doctor if rash occurs

Keep out of reach of children. If product is swalowed, get medical help or contact a Poison Control Center right away.

OTHER SAFETY INFORMATION

Flammable: Do not use near heat, flame or while smoking. Contents under pressure do not puncture or incinerate. Do not store at temperatures above 120°F

Directions

• shake well before use • apply liberally 15 minutes before sun exposure and rub into skin • hold container 4 to 6 inches from the skin to apply • do not spray directly onto face. Spray on hands then apply to face • do not apply in windy conditions • use in a well-ventilated area • reapply: • after 80 minutes of swimming or sweating • immediately after towel drying • at least every 2 hours • Sun Protection Measures. Spending time in the sun increases your risk of skin cancer and early skin aging. To decrease this risk, regularly use a sunscreen with a broad spectrum SPF of 15 or higher and other sun protection measures including: • limit time in the sun, especially from 10 a.m. – 2 p.m. • wear long-sleeved shirts, pants, hats, and sunglasses • children under 6 months: Ask a doctor

Inactive ingredients

Aloe Barbadensis Leaf Extract, Butyrospermum Parkii (Shea) Butter, Helianthus Annuus (Sunflower) Seed Oil, SD Alcohol 40-B, Theobroma Cacao (Cocoa) Seed Butter, Tocopheryl Acetate, VA/Butyl Maleate/Isobornyl Acrylate Copolymer

Other information

• Protect this product from excessive heat and direct sun.

• Avoid spraying on fabrics - could cause discoloration.

Questions or comments?

877-875-5225, 9-5 PST weekdays